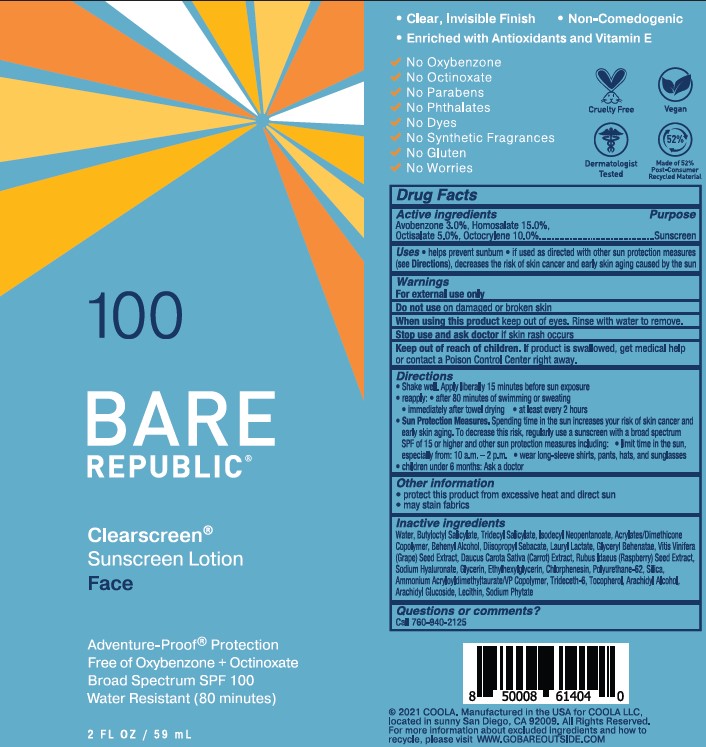 DRUG LABEL: COOLA BARE REPUBLIC CLEARSCREEN SPF100
NDC: 79753-021 | Form: LOTION
Manufacturer: COOLA, LLC
Category: otc | Type: HUMAN OTC DRUG LABEL
Date: 20251215

ACTIVE INGREDIENTS: HOMOSALATE 150 mg/1 mL; AVOBENZONE 30 mg/1 mL; OCTOCRYLENE 100 mg/1 mL; OCTISALATE 50 mg/1 mL
INACTIVE INGREDIENTS: WATER; RASPBERRY SEED OIL; CHLORPHENESIN; HYALURONATE SODIUM; CARROT SEED OIL; .ALPHA.-TOCOPHEROL, DL-; GRAPE SEED OIL; ARACHIDYL ALCOHOL; GLYCERIN; BUTYLOCTYL SALICYLATE; ETHYLHEXYLGLYCERIN; TRIDECYL SALICYLATE; DOCOSANOL; GLYCERYL MONOBEHENATE; TRIDECETH-6; PHYTATE SODIUM; POLYURETHANE-62; LAURYL LACTATE; LECITHIN, SOYBEAN; ARACHIDYL GLUCOSIDE; SILICON DIOXIDE; AMMONIUM ACRYLOYLDIMETHYLTAURATE/VP COPOLYMER; ISODECYL NEOPENTANOATE; DIISOPROPYL SEBACATE; 2-ETHYLHEXYL ACRYLATE, METHACRYLATE, METHYL METHACRYLATE, OR BUTYL METHACRYLATE/HYDROXYPROPYL DIMETHICONE COPOLYMER (30000-300000 MW)

COOLA BARE REPUBLIC CLEARSCREEN SPF100 LOTION

Active ingredients

Avobenzone 3.0%

Homosalate 15.0%

Octisalate 5.0%

Octocrylene 10.0%

Purpose

Sunscreen

Uses

- helps prevent sunburn
- if used as directed with other sun protection measures (see Directions), decreases the risk of skin cancer and early skin aging caused by the sun

Warnings

For external use only

Do not use

- on damaged or broken skin.

When using this product

- keep out of eyes. Rinse with water to remove.

Stop use and ask a doctor if

- rash occurs.

Keep out of the reach of children

If swallowed, get medical help or contact a Poison Control Center right away.

Directions

- apply liberally 15 minutes before sun exposure

- reapply:

-after 80 minutes of swimming or sweating

-immediately after towel drying

-at least every 2 hours

- children under 6 months of age: Ask a doctor
- Sun Protection Measures. Spending time in the sun increases your risk of skin cancer and early skin aging. To decrease this risk, regularly use a sunscreen with a Broad Spectrum SPF value of 15 or higher and other sun protection measures including:

-limit time in the sun, especially from 10 a.m.-2 p.m.

-wear long-sleeved shirts, pants, hats, and sunglasses

Other information

- protect this product from excessive heat and direct sun
- may stain or damage some fabrics, materials or surfaces

Inactive Ingredients

Water, Butyloctyl Salicylate, Tridecyl Salicylate, Isodecyl Neopentanoate, Acrylates/Dimethicone Copolymer, Behenyl Alcohol, Diisopropyl Sebacate, Lauryl Lactate, Glyceryl Behenatae,Vitis Vinifera (Grape) Seed Extract, Daucus Carota Sativa (Carrot) Extract, Rubus Idaeus (Raspberry) Seed Extract, Sodium Hyaluronate, Glycerin, Ethylhexylglycerin, Chlorphenesin, Polyurethane-62, Silica, Ammonium Acryloyldimethyltaurate/VP Copolymer, Trideceth-6, Tocopherol, Arachidyl Alcohol, Arachidyl Glucoside, Lecithin, Sodium Phytate